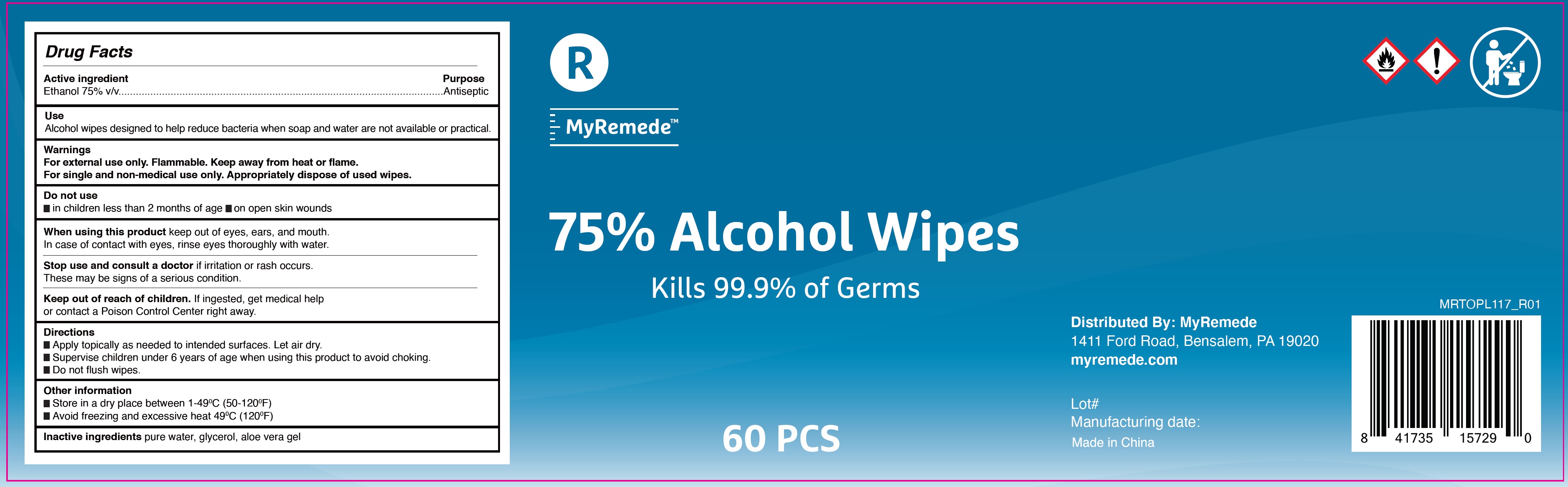 DRUG LABEL: MyRemede 75% Alcohol Wipes
NDC: 77529-002 | Form: CLOTH
Manufacturer: Remede Organics, Inc.
Category: otc | Type: HUMAN OTC DRUG LABEL
Date: 20200826

ACTIVE INGREDIENTS: ALCOHOL 0.75 mL/1 mL
INACTIVE INGREDIENTS: WATER; GLYCERIN; ALOE VERA LEAF

MyRemede 75% Alcohol Wipes

Active ingredient

Ethanol 75% v/v

Purpose

Antiseptic

Use

Alcohol wipes designed to help reduce bacteria when soap and water are not available or practical.

Warnings

For external use only. Flammable. Keep away from heat or flame.
For single and non-medical use only. Appropriately dispose of used wipes.

Do not use

- in children less than 2 months of age
- on open skin wounds

When using this product

keep out of eyes, ears, and mouth. In case of contact with eyes, rinse eyes thoroughly with water.

Stop use and consult a doctor

if irritation or rash occurs. These may be signs of a serious condition.

Keep out of reach of children.

If ingested, get medical help or contact a Poison Control Center right away.

Directions

- Apply topically as needed to intended surfaces. Let air dry.
- Supervise children under 6 years of age when using this product to avoid choking.
- Do not flush wipes

Other information

- Store in a dry place between 1-490C (50-1200F)
- Avoid freezing and excessive heat 490C (1200F)

Inactive ingredients

pure water, glycerol, aloe vera gel